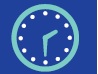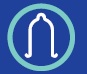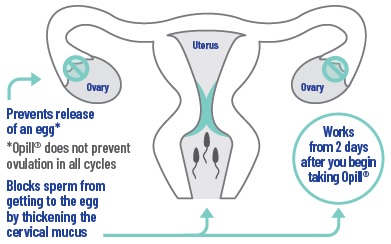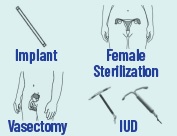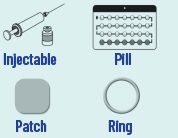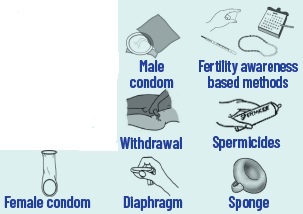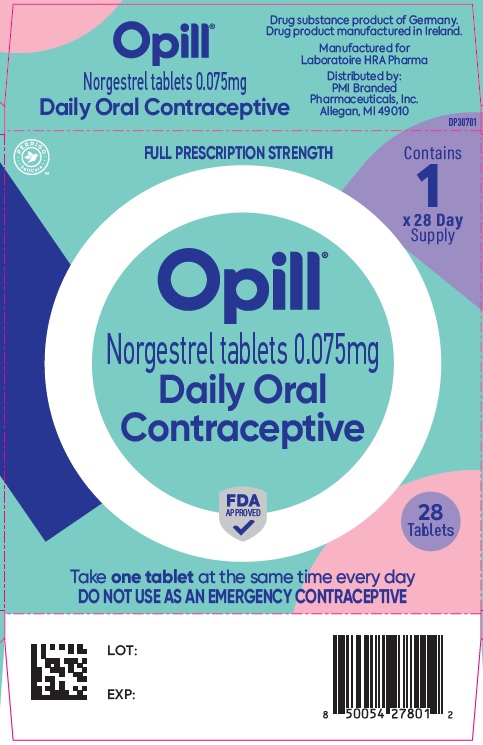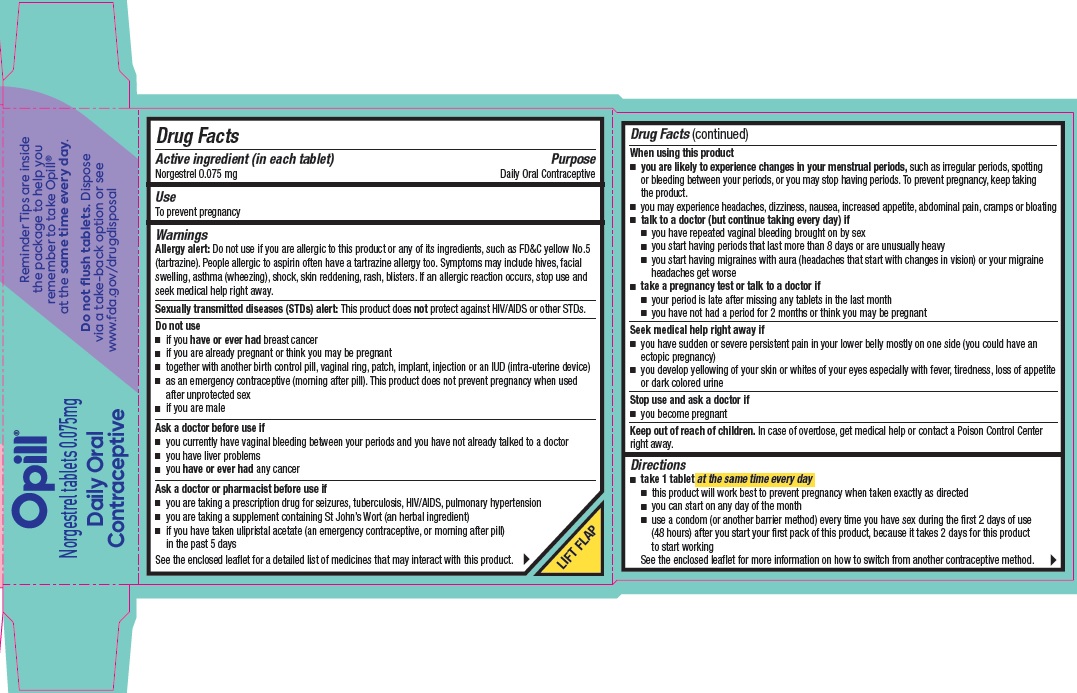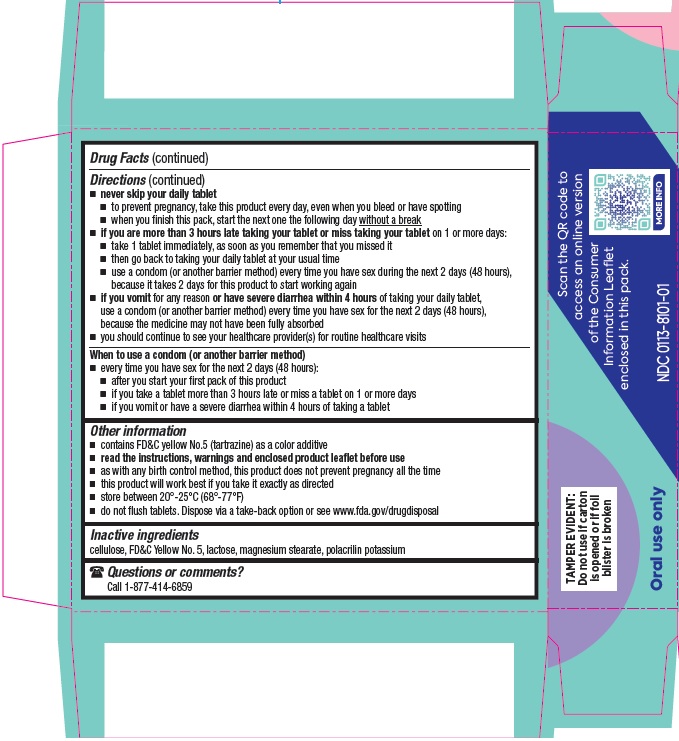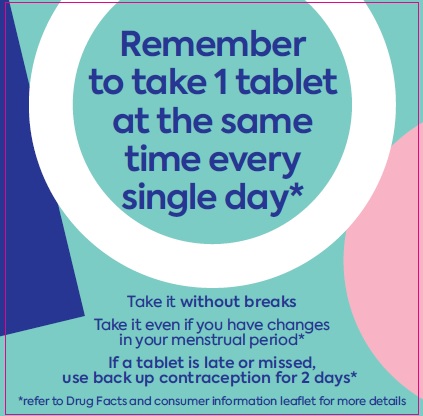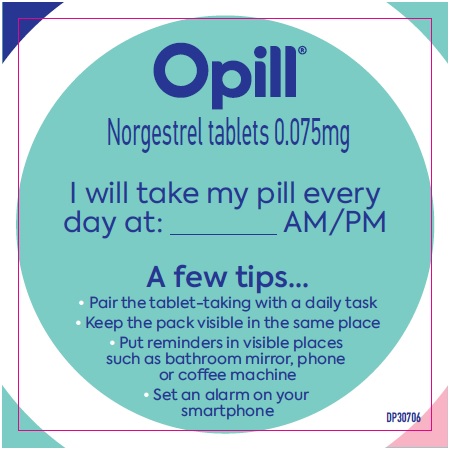 DRUG LABEL: Opill
NDC: 67296-1938 | Form: TABLET
Manufacturer: Redpharm Drug
Category: otc | Type: HUMAN OTC DRUG LABEL
Date: 20251225

ACTIVE INGREDIENTS: NORGESTREL 0.075 mg/1 1
INACTIVE INGREDIENTS: POLACRILIN POTASSIUM; LACTOSE MONOHYDRATE; FD&C YELLOW NO. 5; MAGNESIUM STEARATE; MICROCRYSTALLINE CELLULOSE

Opill®Norgestrel tablets 0.075 mg - Drug Facts

Active ingredient (in each tablet)

Norgestrel 0.075 mg

Purpose

Daily Oral Contraceptive

Use

To prevent pregnancy

Warnings

Allergy alert:Do not use if you are allergic to this product or any of its ingredients, such as FD&C yellow No. 5 (tartrazine). People allergic to aspirin often have a tartrazine allergy too. Symptoms may include hives, facial swelling, asthma (wheezing), shock, skin reddening, rash, blisters. If an allergic reaction occurs, stop use and seek medical help right away.

Sexually transmitted diseases (STDs) alert:This product does notprotect against HIV/AIDS or other STDs.

Do not use

- if you have or ever hadbreast cancer
- if you are already pregnant or think you may be pregnant
- together with another birth control pill, vaginal ring, patch, implant, injection or an IUD (intra-uterine device)
- as an emergency contraceptive (morning after pill). This product does not prevent pregnancy when used after unprotected sex
- if you are male

Ask a doctor before use if

- you currently have vaginal bleeding between your periods and you have not already talked to a doctor
- you have liver problems
- you have or ever hadany cancer

Ask doctor or pharmacist before use if

- you are taking a prescription drug for seizures, tuberculosis, HIV/AIDS, pulmonary hypertension
- you are taking a supplement containing St John’s Wort (an herbal ingredient)
- if you have taken ulipristal acetate (an emergency contraceptive, or morning after pill) in the past 5 days

See the enclosed leaflet for a detailed list of medicines that may interact with this product.

When using this product

- you are likely to experience changes in your menstrual periods,such as irregular periods, spotting or bleeding between your periods, or you may stop having periods. To prevent pregnancy, keep taking the product.
- you may experience headaches, dizziness, nausea, increased appetite, abdominal pain, cramps or bloating
- talk to a doctor (but continue taking every day) if
- you have repeated vaginal bleeding brought on by sex
- you start having periods that last more than 8 days or are unusually heavy
- you start having migraines with aura (headaches that start with changes in vision) or your migraine headaches get worse
- take a pregnancy test or talk to a doctor if
- your period is late after missing any tablets in the last month
- you have not had a period for 2 months or think you may be pregnant

Seek medical help right away if

- you have sudden or severe persistent pain in your lower belly mostly on one side (you could have an ectopic pregnancy)
- you develop yellowing of your skin or whites of your eyes especially with fever, tiredness, loss of appetite or dark colored urine

Stop use and ask a doctor if

- you become pregnant

Keep out of reach of children.

In case of overdose, get medical help or contact a Poison Control Center right away.

Directions

- take 1 tablet at the same time every day
- this product will work best to prevent pregnancy when taken exactly as directed
- you can start on any day of the month
- use a condom (or another barrier method) every time you have sex during the first 2 days of use (48 hours) after you start your first pack of this product, because it takes 2 days for this product to start working

See the enclosed leaflet for more information on how to switch from another contraceptive method.

- never skip your daily tablet
- to prevent pregnancy, take this product every day, even when you bleed or have spotting
- when you finish this pack, start the next one the following day without a break
- if you are more than 3 hours late taking your tablet or miss taking your tableton 1 more days:
- take 1 tablet immediately, as soon as you remember that you missed it
- then go back to taking your daily tablet at your usual time
- use a condom (or another barrier method) every time you have sex during the next 2 days (48 hours), because it takes 2 days for this product to start working again
- if you vomitfor any reason or have severe diarrhea within 4 hoursof taking your daily tablet, use a condom (or another barrier method) every time you have sex for the next 2 days (48 hours), because the medicine may not have been fully absorbed
- you should continue to see your healthcare provider(s) for routine healthcare visits

When to use a condom (or another barrier method)

- every time you have sex for the next 2 days (48 hours):
- after you start your first pack of this product
- if you take a tablet more than 3 hours late or miss a tablet on 1 or more days
- if you vomit or have a severe diarrhea within 4 hours of taking a tablet

Other information

- contains FD&C yellow No. 5 (tartrazine) as a color additive
- read the instructions, warnings and enclosed product leaflet before use
- as with any birth control method, this product does not prevent pregnancy all the time
- this product will work best if you take it exactly as directed
- store between 20°-25°C (68°-77°F)
- do not flush tablets. Dispose via a take-back option or see www.fda.gov/drugdisposal

Inactive Ingredients

cellulose, FD&C Yellow No. 5, lactose, magnesium stearate, polacrilin potassium

Questions or comments?

Call 1-877-414-6859

Consumer information leaflet

Opill®Norgestrel tablets 0.075mg

Daily Oral Contraceptive

FDA APPROVED

What you need to know

Before you use Opill®, read this information carefully and take Opill® exactly as directed.

Keep this leaflet as it contains important information.

DP30705

What this leaflet covers

1. What is Opill®?
2. Is Opill®right for you?
3. How to take Opill®?
4. Tips to help you remember to take Opill®on-time
5. When to talk to a doctor or pharmacist?
6. What could happen to your periods while taking Opill®?
7. Other questions you may have

Before you start…

Two things you need to know.

It’s very important to take Opill®every single day at the same time:

- Without breaks
- Even if you have changes in your menstrual period

same time every day

It takes 2 days for Opill®to start working so use a condom (or other barrier method) every time you have sex for the next 2 days (48 hours):

- After you start your first pack of Opill®
- If you take a tablet more than 3 hours late or miss a tablet on 1 or more days
- If you vomit of have severe diarrhea within 4 hours of taking a tablet

OPILL®WILL WORK BEST IF YOU TAKE IT EXACTLY AS DIRECTED

1. What is Opill®?

Opill®is a daily oral contraceptive(also called a birth control pill) used by women to prevent pregnancy.

Opill®is NOTan emergency contraceptive (morning after pill). You should not take Opill®to try to prevent pregnancy afterunprotected sex because it will not work.

Opill®does NOTprotect against HIV/AIDS or other sexually transmitted diseases (STDs). You should use condoms to protect against HIV/AIDS or other STDs.

1. Is Opill®right for you?

Most women can use Opill®. However, do not use Opill®:

- If you have or ever had breast cancer, because some breast cancers are sensitive to hormones like the one in Opill®.
- If you know that you are already pregnant or think you may be pregnant.
- Together with another birth controlpill, vaginal ring, patch, implant injection or an IUD (intra-uterine device).
- If you are allergic to this product or any of its ingredients, such as the color additive FD&C yellow No. 5 (tartrazine).People allergic to aspirin often have a tartrazine allergy too. Symptoms may include: hives, facial swelling, asthma (wheezing), shock, skin reddening, rash, blisters. If an allergic reaction occurs, stop use and seek medical help right away.

Talk to a doctor before staring Opill®if:

- You currently have vaginal bleeding between your periods and you have not already talked to a doctor, because it could be the sign of a condition that should be treated.
- You have liver tumors or a liver disease.
- You have or ever had any cancer, because some cancers are sensitive to hormones like the one in Opill®.
- How to take Opill®?
- Take 1 tablet at the same time every single day (and no later than 3 hours from the time you took
- your tablet the day before). Never skip your daily tablet.
- Never take a break between packs. When you finish one pack (all 28 tablets), you should start the next pack the following day.
- Take Opill® every single day, even when you have your period, or if you have spotting or bleeding between periods.
- Do not skip tablets even if you do not have sex very often.

To start using Opill®:

- You can start your first pack on any day.
- If you are switching from another oral contraceptive, vaginal ring, or patch,start taking Opill® the day after you stop the other method.
- You must take your daily tablet at the same time of day every single day.
- You must use a condom (or another barrier method)every time you have sex during the first 2 days (48 hours)because it takes 2 days to start working.

What if I am late taking my tablet?

Less than 3 hours late:

Don’t worry. Take 1 tablet immediately and go back to taking your tablet at your usual time the following day.

More than 3 hours late OR you missed one or more tablets:

- Take 1 tablet immediately, as soon as you remember.
- Then, go back to taking your tablet at your usual time. This means you may take 2 tablets in 1 days.
  - For example, if you usually take your tablet at night, but forget and remember in the morning, take 1 tablet when you remember andtake 1 tablet again at the usual time that night.
- You must use a condom (or another barrier method)every time you have sex during the 2 days (48 hours)after you restart Opill®, because it takes 2 days to start working again.
- Take a pregnancy test or talk to a doctorif your period is later after missing any tablets in the last month.

What if I vomit or have severe diarrhea within 4 hours of taking my tablet?

- Use a condom (or another barrier method)every time you have sex for the next 2 days (48 hours)because the medicine may not have been fully absorbed.
- The next day, take your daily tablet at your usual time.
- Tips to help you remember to take Opill®on-time

Choose a convenient time of day.It is best to link this to something you already do at the same time every day.For example, when you wake up or when you brush your teeth.

Set reminders.Consider using your smartphone to set a daily alarm, and put reminders in visible places such as bathroom mirror, phone or coffee machine.

Buy a new pack of Opill®before finishing the pack so you can start the next pack on time.

1. When to talk to a doctor or pharmacist?

What if I am taking other medicines or herbal products?

Talk to a doctor or pharmacistif you are taking or start to take any of the following medications, as these may make Opill®less effective:

- Certain drugs to treat
- - Seizures (barbiturates, carbamazepine, oxcarbazepine, phenytoin, topiramate, primidone)
- - Tuberculosis (rifampin, rifabutin)
- - Pulmonary hypertension (bosentan)
- - HIV/AIDS (efavirenz)
- St. John’s Wort (or any herbal products containing hypericum perforatum)

Your doctor or pharmacist may advise you to use another form of contraception.

What if I have taken an emergency contraceptive (morning after pill) before starting Opill®?

- Talk to a doctor or pharmacistif you have taken an emergency contraceptive in the past 5 days.
- Opill®should not be used for 5 days after using the emergency contraceptive ella®which contains ulipristal acetate. This might reduce the ability of both Opill®and ella®to prevent pregnancy. Also, use a condom (or another barrier method)every time you have sex until your next period.

What if I have sudden or severe persistent pain in my lower belly mostly on one side?

Seek medical help right away.

You may have an ectopic pregnancy (a fertilized egg implanted in the wrong place).

While ectopic pregnancy is unlikely if you are taking Opill®as directed, it is a serious risk if it occurs. Severe persistent belly pain may occur for a few reasons and should be assessed right away.

What if I become pregnant while taking Opill®?

- Stop taking this product and talk to a doctorif you get pregnant while taking Opill®.
- Signs that you may be pregnant might include: missed periods, tender breasts, feeling nauseous, fatigue, and/or needing to urinate urgently or more frequently.
- Take a pregnancy test or talk to a doctorif you period is late after missing any tablets in the last month, if you have not had a period for 2 months, or if you think you may be pregnant.

What if I get migraines while using Opill®?

If you start having migraines with aura (headaches that start with changes in vision)or your migraine headaches get worse, talk to a doctor but continue taking every day.Some women with migraine may be at increased risk of stroke.

What if I develop yellowing of skin or eyes while using Opill®?

Seek medical help right awayif you develop the following rare symptoms: yellowing of the whites of your eyes or skin (especially with fever, tiredness, loss of appetite or dark colored urine).These may be a sign of liver problems which can be a serious medical condition.

1. What could happen to your periods while taking Opill®?

What changes in my menstrual period are normal while using Opill®?

Most changes to periods are to be expected.

Continue taking Opill®exactly as directed, even if you have the following changes in your periods:

- Your periods may be less or more frequent, shorter or longer, lighter or heavier than before you started Opill®. You may also have some spotting or bleeding between periods.
- Some women stop having periods while taking Opill®.
- Take a pregnancy test or talk to a doctorif you period is late after missing any tablets in the last month, if you have not had a period of 2 months, or if you think you may be pregnant. Signs that you may be pregnant are listed in section 5, under « What if I become pregnant while taking Opill.

What changes to my period are NOTexpected when using Opill®?

Talk to a doctor AND continue taking this product every dayif you experience any of the following:

- You repeatedly have vaginal bleeding that is brought on by sex.
- You start having menstrual periods that last more than 8 days or are unusually heavy.
- Other questions you may have

What type of oral contraceptive is Opill®?

- Opill®is a progestin-only pill (POP)
- Opill®contains the hormone progestin but does not contain estrogen, so it is different than the commonly used combined oral contraceptive, which contains both estrogen and progestin.
  Opill®works mainly by thickening your cervical mucus which helps to block sperm from getting to the egg. You must take it every day to prevent pregnancy. In addition, Opill®may prevent your ovaries from releasing eggs.
- Every one of the 28 tablets in your blister pack contains the active ingredient so you must take one tablet every day with no breaks.

How effective is Opill®at preventing pregnancy?

- As with any birth control method, Opill®does not prevent pregnancy all the time. Opill®will work best if you take it exactly as directed.
- In 8 US clinical trials, approximately 98 out of 100 sexually active women who used Opill®for a year did not become pregnant in that time.

What if I decide I want to get pregnant?

- If you decide you want to become pregnant, simply stop taking Opill®. Opill®will not delay your ability to get pregnant.

Is it okay to use Opill®if I’m breastfeeding?

- Yes. Opill®is safe and effective in breastfeeding women. Small amounts of progestin may pass into the breast milk; however, no adverse effects have been found on either breastfeeding performance or infant health.

What types of side effects may I expect while using Opill®?

- When used as directed, Opill®is safe and effective.
- The most common side effect is changes in menstrual periods (bleeding). See section 6.
- Less common side effects may include headaches, dizziness, nausea, increased appetite, abdominal pain, cramps or bloating.

Routine healthcare

You should continue to see your healthcare provider(s) for routine healthcare visits.

- It is important that you continue to have regular Pap smear tests (cervical screening) while taking Opill®.
- Regular breast screening (mammography) is also recommended.
- If you are worried you may have a Sexually Transmitted Disease (STS) including HIV (AIDS), see your healthcare provider as soon as you can. Many STDs, like HIV, have no symptoms at all. The only way to know for sure that you do not have an STD is to get tested. Only barrier methods (such as condoms) can protect you from STD.

You should tell your healthcare provider(s) that you are taking Opill®.

Regular contraception

There are many different types of contraception available, and you should be able to find the right method for you. The different contraceptive options are listed below from the most effective to the least effective. You can ask your healthcare provider(s) for advice.

 |  | How to make your method most effective
Tier 1; More Effective; Less than 1 pregnancy per 100 women in one year |  | After procedure, little or nothing to do or remember; Vasectomy:Use another method for first 3 months
Tier 2; 4-7 pregnancies per 100 women in one year |  | Injectable:Get repeat injections on time; Pills:Take a pill each day; Patch, ring:Keep in place, change on time
Tier 3; Less Effective; More than 13 pregnancies per 100 women in one year |  | Condoms, sponge, withdrawal, spermicides, diaphragm:; Use correctly every time you have sex; Fertility awareness-based methods:Abstain or use condoms on fertile days. Newer methods (Standard Days, Natural Cycles, and Symptothermal may be easier to use and consequently more effective).

Trussell J, Aiken ARA, Micks E, Guthrie KA. Efficacy, safety, and personal considerations. In: Hatcher RA, Nelson AL, Trussell J, Cwiak C, Cason P, Policar MS, Edelman A, Aiken ARA, Marrazzo J, Kowal D, eds. Contraceptive technology. 21sted. New York, NY: Ayer Company Publishers, Inc., 2018

More about routine healthcare and contraception

For further information on all methods of contraception or screening, go to

- https://www.cdc.gov/reproductivehealth/contraception/index.htm
- https://www.cdc.gov/cancer/breast/basic_info/screening.htm
- https://www.cdc.gov/cancer/cervical/basic_info/screening.htm

What if I still have questions about Opill®?

If you have questions or need more information, call our toll-free number: 1-877-414-6859

Reminder card Front –

Remember to take 1 tablet at the same time every single day*

Take it without breaks

Take is even if you have changes in your menstrual period*

If a tablet is late or missed, use back up contraception for 2 days*

*refer to Drug Facts and consumer information leaflet for more details

Reminder card Back –

Opill®

Norgestrel tablets 0.075mg

I will take my pill every day at: _________AM/PM

A few tips…

- Pair the tablet-taking with a daily task
- Keep the pack visible in the same place
- Put reminders in visible places such as bathroom mirror, phone or coffee machine
- Set an alarm on your smartphone

DP30706

Package/Label Principal Display Panel

PERRIGO Selfcare™

FULL PRESCRIPTION STRENGTH

Contains 1 x 28 Day Supply

Opill®

Norgestrel tablets 0.075mg

Daily Oral Contraceptive

FDA APPROVED

28 Tablets

Take one tablet at the same time every day

DO NOT USE AS AN EMERGENCY CONTRACEPTIVE